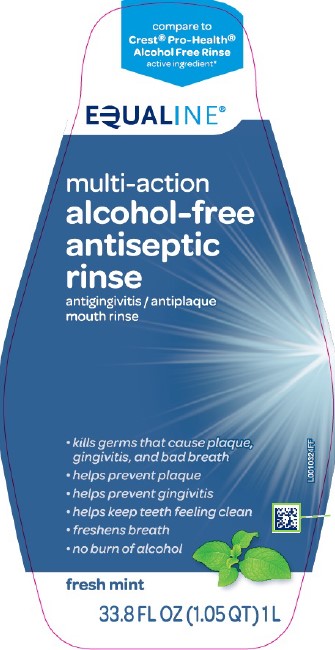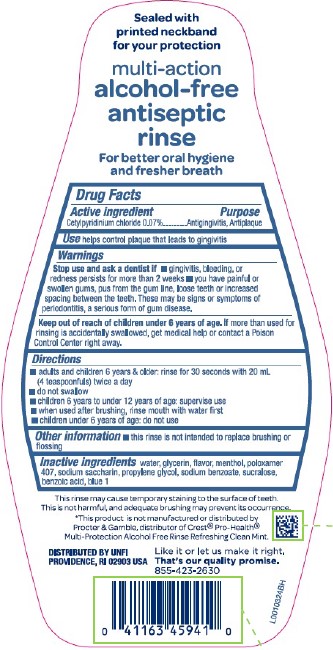 DRUG LABEL: Equaline Multi-Action Antiseptic
NDC: 41163-299 | Form: RINSE
Manufacturer: United Natural Foods, Inc. dba UNFI
Category: otc | Type: HUMAN OTC DRUG LABEL
Date: 20260217

ACTIVE INGREDIENTS: CETYLPYRIDINIUM CHLORIDE 0.7 mg/1 mL
INACTIVE INGREDIENTS: GLYCERIN; MENTHOL, UNSPECIFIED FORM; POLOXAMER 407; SACCHARIN SODIUM; PROPYLENE GLYCOL; SODIUM BENZOATE; SUCRALOSE; WATER; BENZOIC ACID; FD&C BLUE NO. 1

Equaline 299.006/299AM
Multi Action Alcohol Free Antiseptic Rinse w/CPC

Tamper Evident Statement

Sealed with printed neckband for your protection

Claims

multi-action alcohol-free antiseptic rinse

For better oral hygiene and fresher breath

Active ingredient

Cetylpyridinium chloride 0.07%

Purpose

Antigingivitis, Antiplaque

Use

helps control plaque that leads to gingivitis

Warnings

for this product

Stop use and ask a dentist if

- gingivitis, bleeding, or redness persists for ore than 2 weeks
- you have painful or swollen gums, pus from the gum line, loose teeth or increased spacing between the teeth. These may be signs or symptoms of periodontitis, a serious form of gum disease.

Keep out of reach of children under 6 years of age.

If more than used for rinsing is accidentally swallowed, get medical help or contact a Poison Control Center right away.

Directions

- adults and children 6 years & older: rinse for 30 seconds with 20 mL (4 teaspoonfuls) twice a day
- do not swallow
- children 6 years to under 12 years of age: supervise use
- when used after brushing, rinse mouth with water first
- children under 6 years of age: do not use

Other information

- this rinse is not intended to replace brushing or flossing

inactive ingredients

water, glycerin, flavor, menthol, poloxamer 407, sodium saccharin, propylene glycol, sodium benzoate, sucralose, benzoic acid, blue 1

Disclaimers

This rinse may cause temporary staining to the surface of teeth.

This is not harmful and adequate brushing may prevent its occurrence.

*This product is not manufactured or distributed by Procter & Gamble, distributor of Crest®Pro-Health®Multi-Protection Alcool Free Rinse Refreshing Clean Mint.

ADVERSE REACTION

DISTRIBUTED BY UNFI

PROVIDENCE, RI 02903 USA

Like it or let us make it right.

That's our quality promise.

855-423-2630

Principal display panel

compare to Crest®Pro-Health®Alcohol Free Rinse active ingredient*

EQUALINE®

multi-action

alcohol-free

antiseptic rinse

antigingivitis/antiplaque

mouth rinse

- kills germs that cause plaque, gingivitis, and bad breath
- helps prevent plaque
- helps prevent gingivitis
- helps keep teeth feeling clean
- freshens breath
- no burn of alcohol

fresh mint

33.8 FL OZ (1.05 QT) 1 L